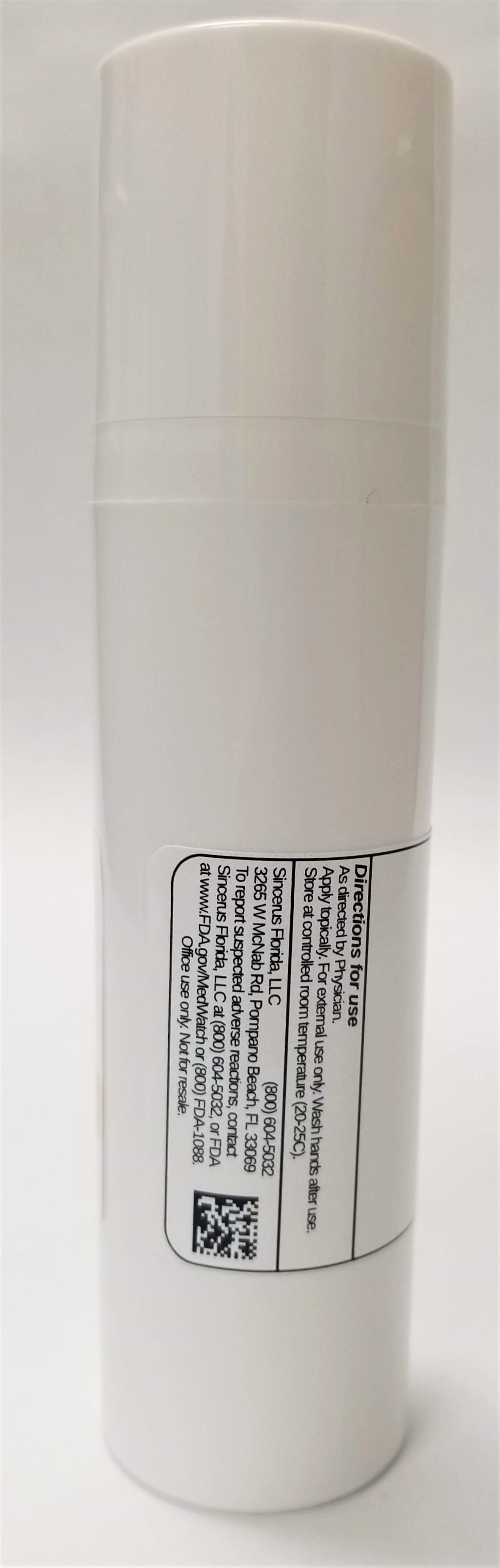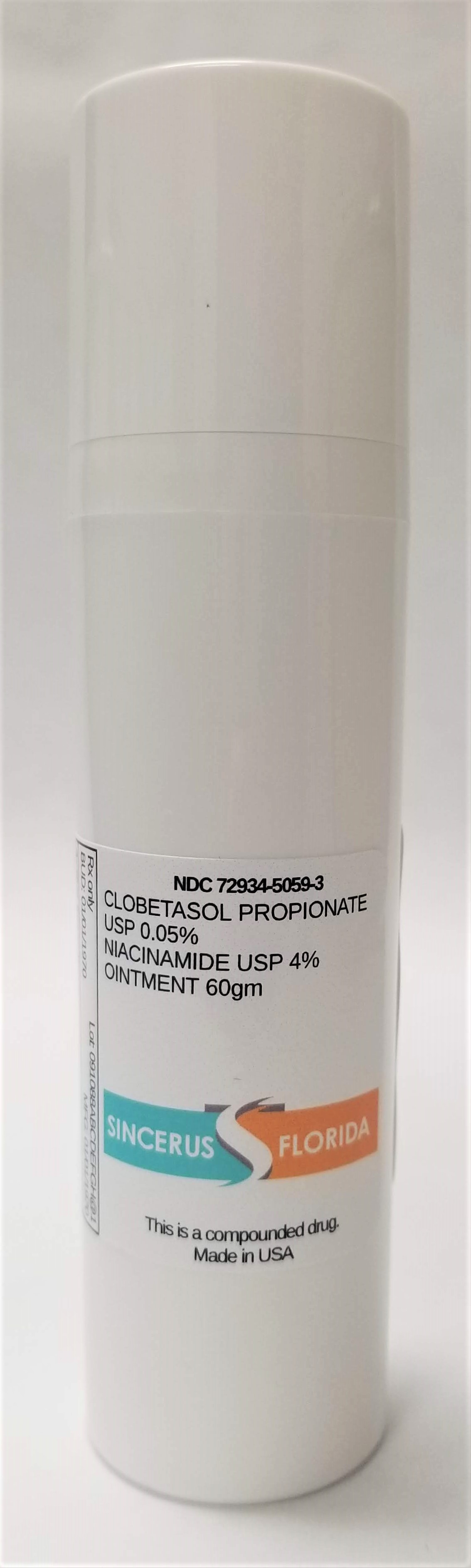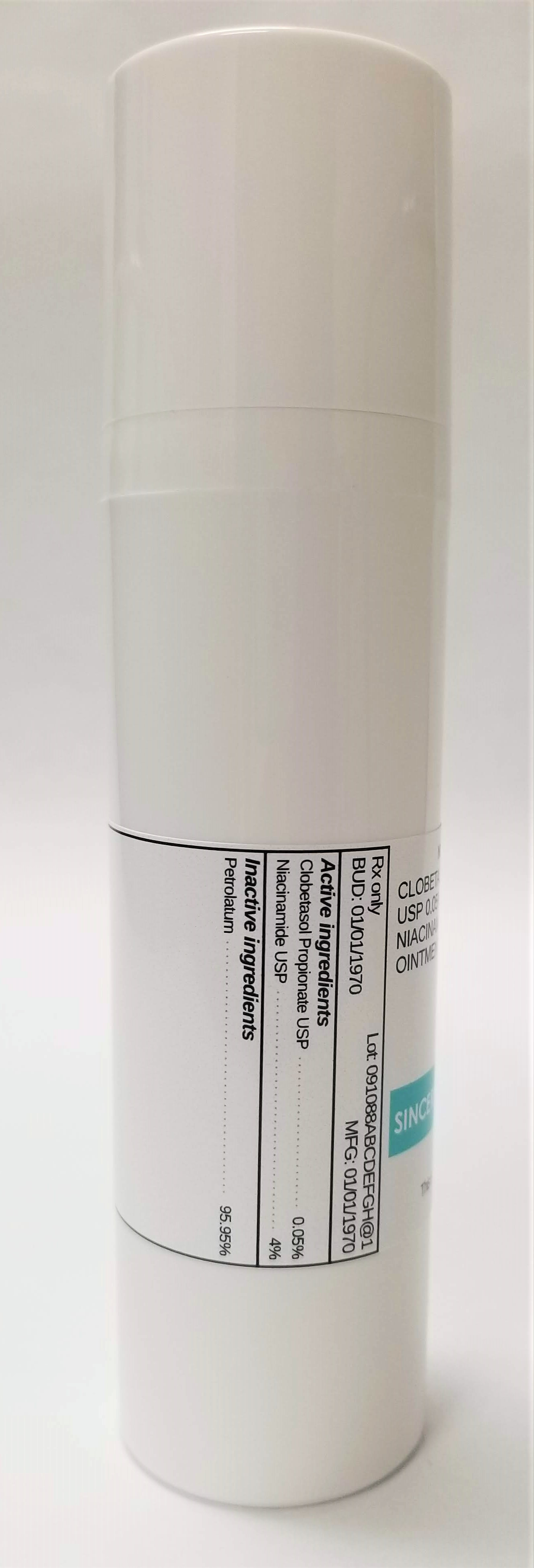 DRUG LABEL: CLOBETASOL PROPIONATE 0.05% / NIACINAMIDE 4%
NDC: 72934-5059 | Form: OINTMENT
Manufacturer: Sincerus Florida, LLC
Category: prescription | Type: HUMAN PRESCRIPTION DRUG LABEL
Date: 20190502

ACTIVE INGREDIENTS: NIACINAMIDE 4 g/100 g; CLOBETASOL PROPIONATE 0.05 g/100 g

CLOBETASOL PROPIONATE 0.05% / NIACINAMIDE 4%